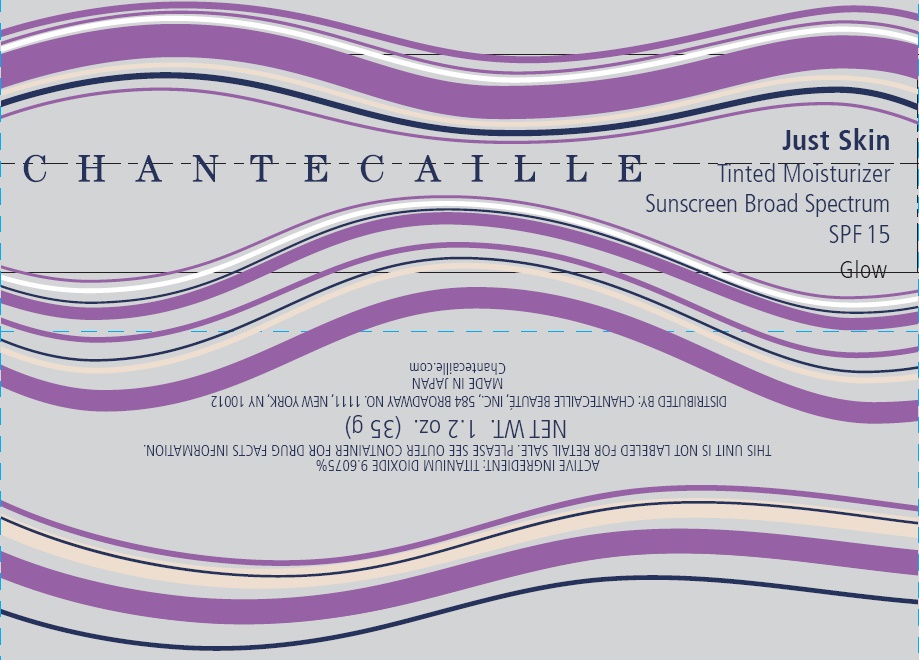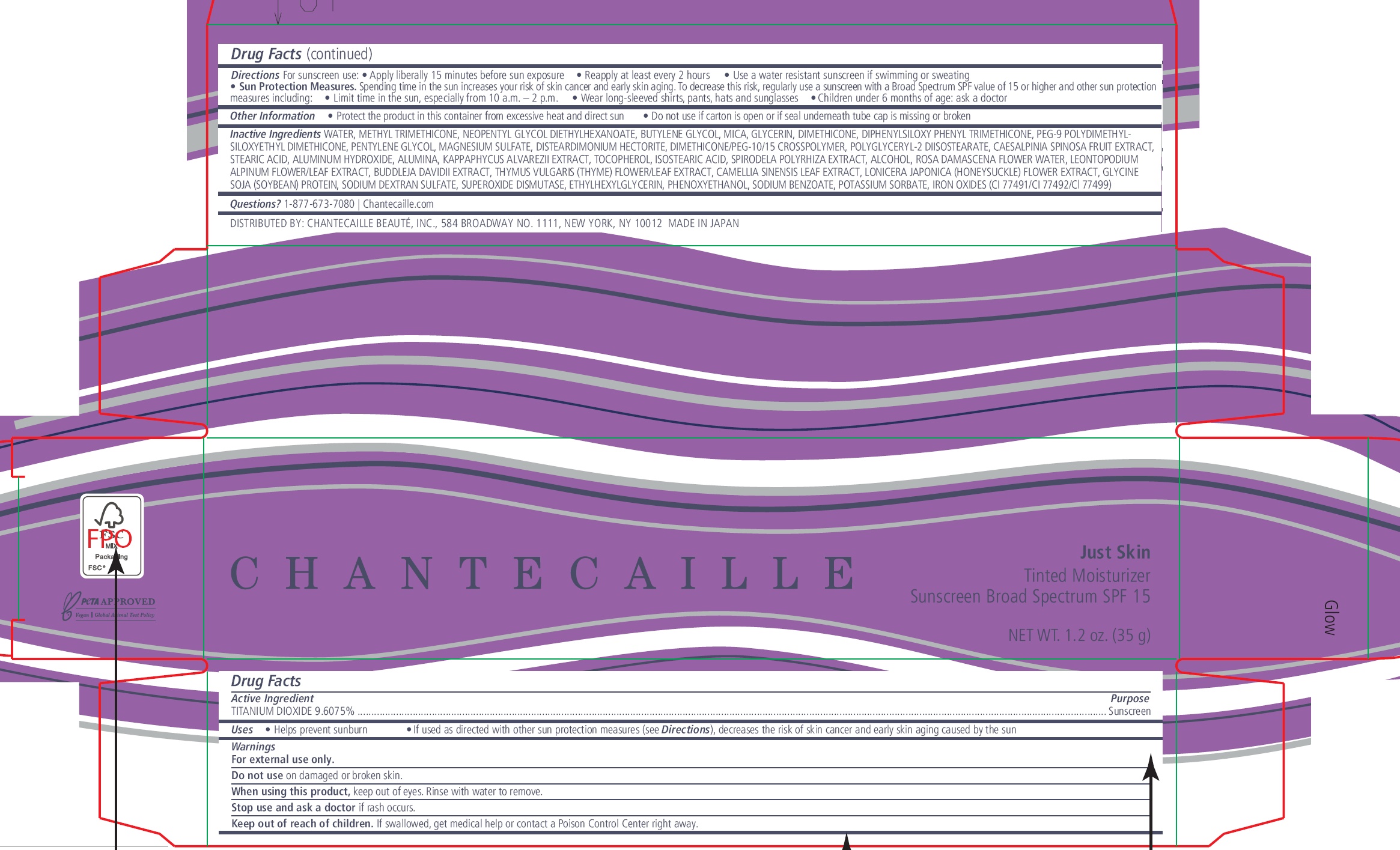 DRUG LABEL: Chantecaille Just Skin Tinted Moisturizer Sunscreen Broad Spectrum SPF 15 Glow
NDC: 42893-036 | Form: CREAM
Manufacturer: Chantecaille Beaute Inc
Category: otc | Type: HUMAN OTC DRUG LABEL
Date: 20240424

ACTIVE INGREDIENTS: TITANIUM DIOXIDE 96.075 mg/1 g
INACTIVE INGREDIENTS: WATER; METHYL TRIMETHICONE; NEOPENTYL GLYCOL DIETHYLHEXANOATE; BUTYLENE GLYCOL; MICA; GLYCERIN; DIMETHICONE; DIPHENYLSILOXY PHENYL TRIMETHICONE; PEG-9 POLYDIMETHYLSILOXYETHYL DIMETHICONE; PENTYLENE GLYCOL; MAGNESIUM SULFATE, UNSPECIFIED FORM; DISTEARDIMONIUM HECTORITE; DIMETHICONE/PEG-10/15 CROSSPOLYMER; POLYGLYCERYL-2 DIISOSTEARATE; STEARIC ACID; ALUMINUM HYDROXIDE; ALUMINUM OXIDE; KAPPAPHYCUS ALVAREZII; TOCOPHEROL; ISOSTEARIC ACID; ALCOHOL; ROSA X DAMASCENA FLOWER OIL; LEONTOPODIUM NIVALE SUBSP. ALPINUM FLOWERING TOP; THYME; GREEN TEA LEAF; LONICERA JAPONICA FLOWER; SOYBEAN; SUPEROXIDE DISMUTASE (SACCHAROMYCES CEREVISIAE); ETHYLHEXYLGLYCERIN; PHENOXYETHANOL; SODIUM BENZOATE; POTASSIUM SORBATE; FERRIC OXIDE RED

Chantecaille Just Skin Tinted Moisturizer Sunscreen Broad Spectrum SPF 15 Glow

Active Ingredient

TITANIUM DIOXIDE 9.6075%

Purpose

Sunscreen

Uses

- Helps prevent sunburn
- If used as directed with other sun protection measures (see Directions), decreases the risk of skin cancer and early skin aging caused by the sun

Warnings

For external use only.

Do not use

on damaged or broken skin.

When using this product,

keep out of eyes. Rinse with water to remove.

Stop use and ask a doctor

if rash occurs.

Keep out of reach of children.

If swallowed, get medical help or contact a Poison Control Center right away.

Directions

For sunscreen use:

- Apply liberally 15 minutes before sun exposure
- Reapply at least every 2 hours
- Use a water resistant sunscreen if swimming or sweating
- Sun Protection Measures. Spending time in the sun increases your risk of skin cancer and early skin aging. To decrease this risk, regularly use a sunscreen with a Broad Spectrum SPF value of 15 or higher and other sun protection measures including:
- Limit time in the sun, especially from 10 a.m. – 2 p.m.
- Wear long-sleeved shirts, pants, hats and sunglasses
- Children under 6 months of age: ask a doctor

Other Information

- Protect the product in this container from excessive heat and direct sun
- Do not use if carton is open or if seal underneath tube cap is missing or broken

Inactive Ingredients

WATER, METHYL TRIMETHICONE, NEOPENTYL GLYCOL DIETHYLHEXANOATE, BUTYLENE GLYCOL, MICA, GLYCERIN, DIMETHICONE, DIPHENYLSILOXY PHENYL TRIMETHICONE, PEG-9 POLYDIMETHYLSILOXYETHYL DIMETHICONE, PENTYLENE GLYCOL, MAGNESIUM SULFATE, DISTEARDIMONIUM HECTORITE, DIMETHICONE/PEG-10/15 CROSSPOLYMER, POLYGLYCERYL-2 DIISOSTEARATE, CAESALPINIA SPINOSA FRUIT EXTRACT, STEARIC ACID, ALUMINUM HYDROXIDE, ALUMINA, KAPPAPHYCUS ALVAREZII EXTRACT, TOCOPHEROL, ISOSTEARIC ACID, SPIRODELA POLYRHIZA EXTRACT, ALCOHOL, ROSA DAMASCENA FLOWER WATER, LEONTOPODIUM ALPINUM FLOWER/LEAF EXTRACT, BUDDLEJA DAVIDII EXTRACT, THYMUS VULGARIS (THYME) FLOWER/LEAF EXTRACT, CAMELLIA SINENSIS LEAF EXTRACT, LONICERA JAPONICA (HONEYSUCKLE) FLOWER EXTRACT, GLYCINE SOJA (SOYBEAN) PROTEIN, SODIUM DEXTRAN SULFATE, SUPEROXIDE DISMUTASE, ETHYLHEXYLGLYCERIN, PHENOXYETHANOL, SODIUM BENZOATE, POTASSIUM SORBATE, IRON OXIDES (CI 77491/CI 77492/Cl 77499)

Questions?

1-877-673-7080 Chantecaille.com